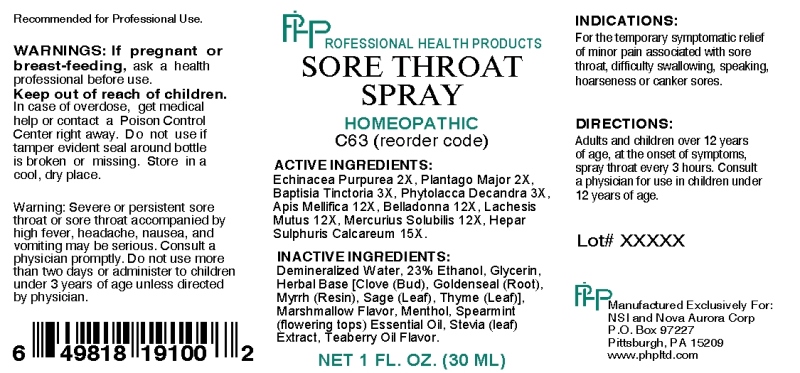 DRUG LABEL: Sore Throat
NDC: 53173-0001 | Form: SPRAY
Manufacturer: Nova Aurora Corp
Category: homeopathic | Type: HUMAN OTC DRUG LABEL
Date: 20151009

ACTIVE INGREDIENTS: ECHINACEA PURPUREA 2 [hp_X]/1 mL; PLANTAGO MAJOR 2 [hp_X]/1 mL; BAPTISIA TINCTORIA ROOT 3 [hp_X]/1 mL; PHYTOLACCA AMERICANA ROOT 3 [hp_X]/1 mL; APIS MELLIFERA 12 [hp_X]/1 mL; ATROPA BELLADONNA 12 [hp_X]/1 mL; LACHESIS MUTA VENOM 12 [hp_X]/1 mL; MERCURIUS SOLUBILIS 12 [hp_X]/1 mL; CALCIUM SULFIDE 15 [hp_X]/1 mL
INACTIVE INGREDIENTS: CLOVE; GOLDENSEAL; MYRRH; SAGE; THYME; GLYCERIN; WATER; ALCOHOL; MENTHOL; METHYL SALICYLATE; STEVIA REBAUDIUNA LEAF; SPEARMINT OIL

DRUG FACTS:

ACTIVE INGREDIENTS:

Echinacea Purpurea 2X, Plantago Major 2X, Baptisia Tinctoria 3X, Phytolacca Decandra 3X, Apis Mellifica 12X, Belladonna 12X, Lachesis Mutus 12X, Mercurius Solubilis 12X, Hepar Sulphuris Calcareum 15X.

INDICATIONS:

For the temporary symptomatic relief of minor pain associated with sore throat, difficulty swallowing, speaking, hoarseness or canker sores.

WARNINGS:

If pregnant or breast-feeding, ask a health professional before use.

Keep out of reach of children. In case of overdose, get medical help or contact a Poison Control Center right away.

Do not use if tamper evident seal is broken or missing.

Store in a cool, dry place.

WARNING: Severe or persistent sore throat or sore throat accompanied by high fever, headache, nausea, and vomiting may be serious. Consult a physician promptly. Do not use more than two days or administer to children under 3 years of age unless directed by a physician.

Recommended for Professional Use.

Keep out of reach of children. In case of overdose, get medical help or contact a Poison Control Center right away.

DIRECTIONS:

Adults and children over 12 years of age, at the onset of symptoms, spray throat every 3 hours. Consult a physician for use in children under 12 years of age.

INDICATIONS:

For the temporary symptomatic relief of minor pain associated with sore throat, difficulty swallowing, speaking, hoarseness or canker sores.

INACTIVE INGREDIENTS:

Demineralized Water, 23% Ethanol, Glycerin, Herbal Base [Clove (Flower), Goldenseal (Root), Myrrh (Resin), Sage (Leaf), Thyme (Leaf)], Marshmallow Flavor, Menthol, Spearmint Oil (flowering tops), Stevia (leaf) Extract, Teaberry Oil Flavor.

QUESTIONS:

Manufactured Exclusively For:

NSI and Nova Aurora Corp

P.O. Box 97227

Pittsburgh, PA 15209

www.phpltd.com

PACKAGE LABEL DISPLAY:

PROFESSIONAL HEALTH PRODUCTS

SORE THROAT

SPRAY

HOMEOPATHIC

C63 (reorder code)

NET 1 FL. OZ. (30 ML)